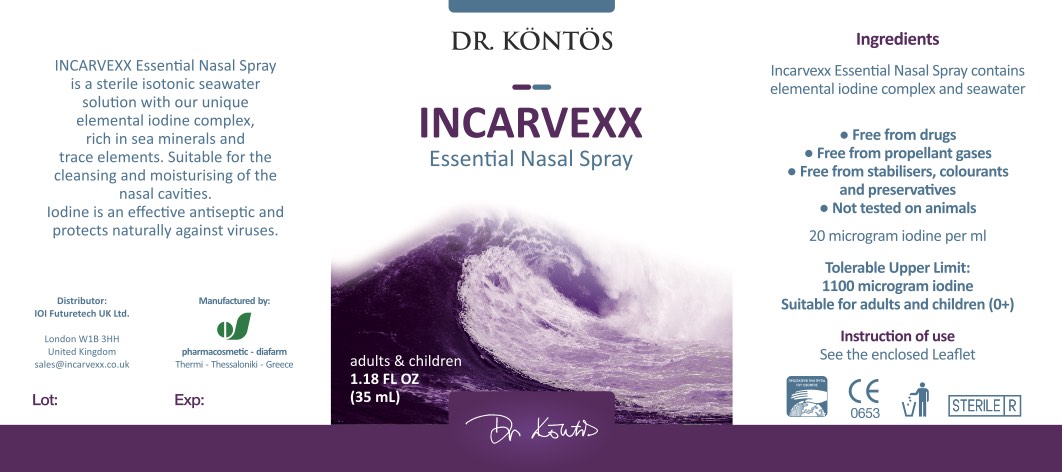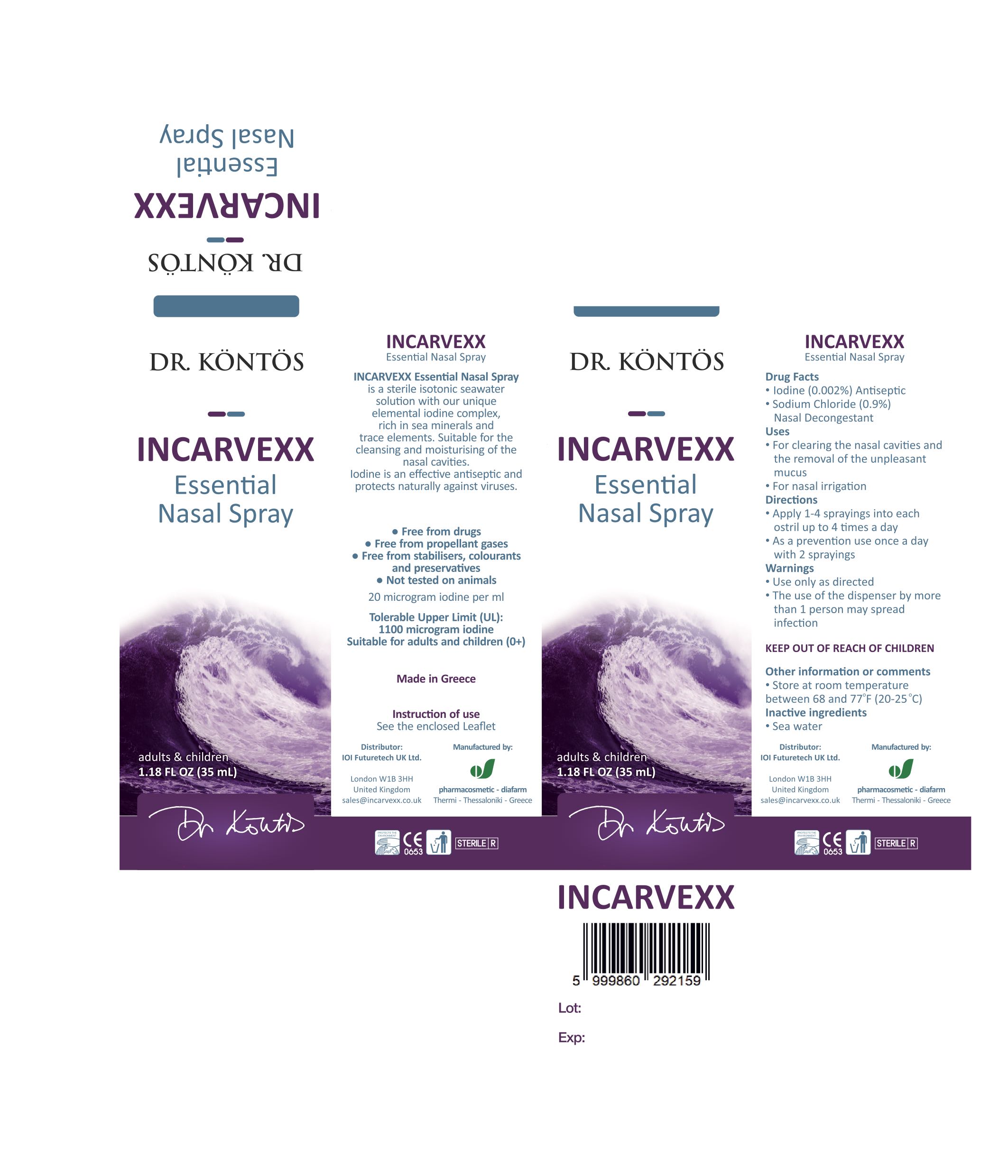 DRUG LABEL: Incarvexx Essential
NDC: 80897-030 | Form: SPRAY
Manufacturer: Nobu Baby LLC
Category: otc | Type: HUMAN OTC DRUG LABEL
Date: 20230110

ACTIVE INGREDIENTS: IODINE 20 ug/1 mL; SODIUM CHLORIDE 9 mg/1 mL
INACTIVE INGREDIENTS: WATER

Incarvexx Essential Nasal Spray

ACTIVE INGREDIENT

lodine (0.002%)

Sodium Chloride (0.9%)

PURPOSE

lodine (0.002%) Antiseptic

Sodium Chloride (0.9%) Nasal Decongestant

Uses

- For clearing the nasal cavities and the removal of the unpleasant mucus
- For nasal irrigation

Directions

* Apply 1-4 sprayings into each nostril up to 4 times a day

* As a prevention use once a day with 2 sprayings

Keep out of reach of children

Warnings

* Use only as directed

* The use of the dispenser by more than 1 person may spread infection

INACTIVE INGREDIENT

- Sea water

Other information or comments

* Store at room temperature between 68 and 77°F (20-25 °C)

PACKAGE LABEL

NDC: 80897-030-35